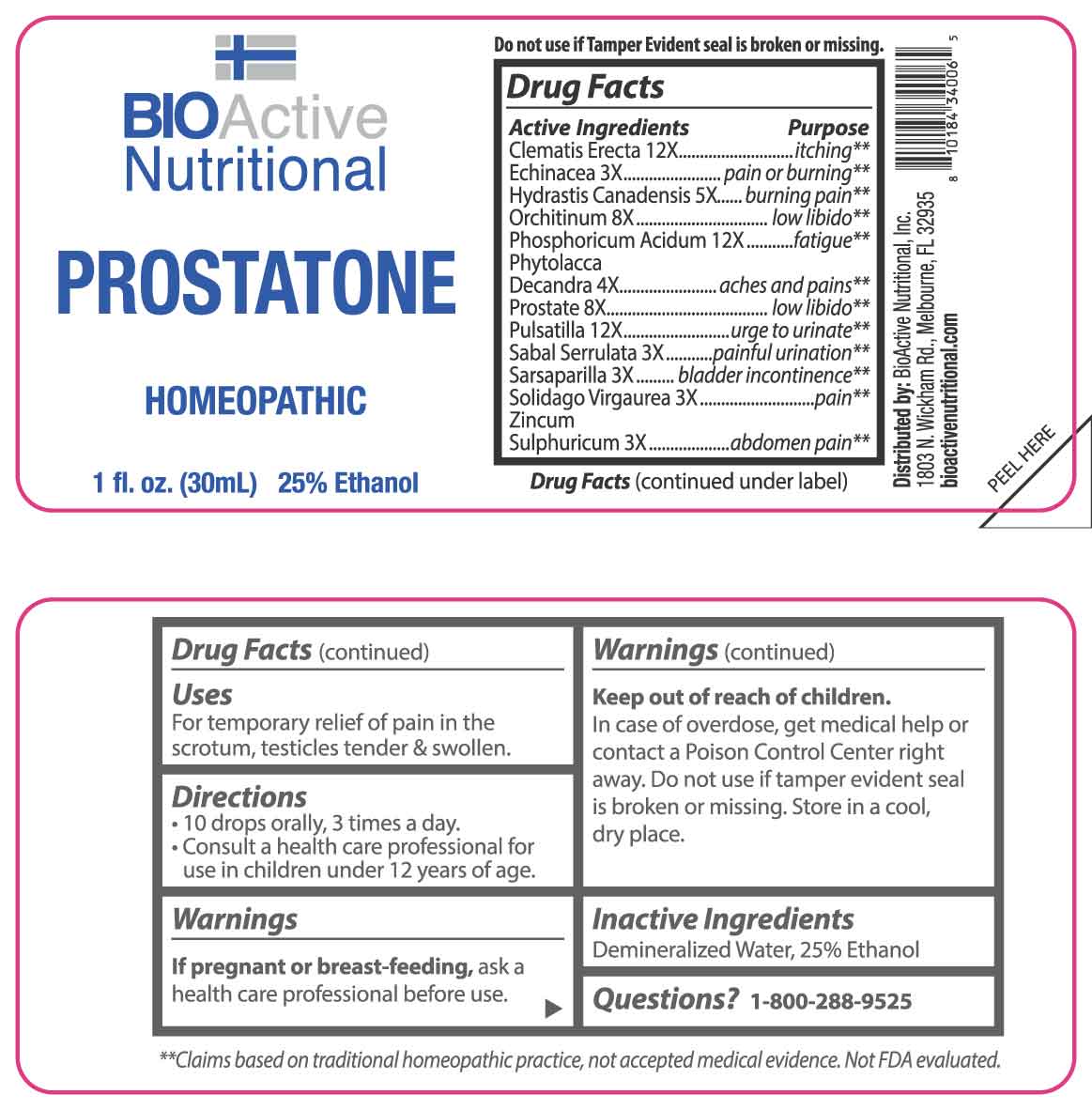 DRUG LABEL: Prostatone
NDC: 43857-0492 | Form: LIQUID
Manufacturer: BioActive Nutritional, Inc.
Category: homeopathic | Type: HUMAN OTC DRUG LABEL
Date: 20250401

ACTIVE INGREDIENTS: ECHINACEA ANGUSTIFOLIA WHOLE 3 [hp_X]/1 mL; SAW PALMETTO 3 [hp_X]/1 mL; SMILAX ORNATA ROOT 3 [hp_X]/1 mL; SOLIDAGO VIRGAUREA FLOWERING TOP 3 [hp_X]/1 mL; ZINC SULFATE HEPTAHYDRATE 3 [hp_X]/1 mL; PHYTOLACCA AMERICANA ROOT 4 [hp_X]/1 mL; GOLDENSEAL 5 [hp_X]/1 mL; SUS SCROFA TESTICLE 8 [hp_X]/1 mL; SUS SCROFA PROSTATE 8 [hp_X]/1 mL; CLEMATIS RECTA FLOWERING TOP 12 [hp_X]/1 mL; PHOSPHORIC ACID 12 [hp_X]/1 mL; PULSATILLA VULGARIS WHOLE 12 [hp_X]/1 mL
INACTIVE INGREDIENTS: WATER; ALCOHOL

DRUG FACTS:

ACTIVE INGREDIENTS:

Clematis Erecta 12X, Echinacea 3X, Hydrastis Canadensis 5X, Orchitinum 8X, Phosphoricum Acidum 12X, Phytolacca Decandra 4X, Prostate 8X, Pulsatilla 12X, Sabal Serrulata 3X, Sarsaparilla 3X, Solidago Virgaurea 3X, Zincum Sulphuricum 3X.

PURPOSE:

Clematis Erecta - itching,** Echinacea – pain or burning,** Hydrastis Canadensis – burning pain,** Orchitinum – low libido,** Phosphoricum Acidum - fatigue,** Phytolacca Decandra – aches and pains,** Prostate – low libido,** Pulsatilla – urge to urinate,** Sabal Serrulata – painful urination,** Sarsaparilla – bladder incontinence,** Solidago Virgaurea - pain,** Zincum Sulphuricum – abdomen pain**

**Claims based on traditional homeopathic practice, not accepted medical evidence. Not FDA evaluated.

USES:

For temporary relief of pain in the scrotum, testicles tender & swollen.

WARNINGS:

If pregnant or breast-feeding, ask a health care professional before use.

Keep out of reach of children. In case of overdose, get medical help or contact a Poison Control Center right away.

Do not use if tamper evident seal is broken or missing.

Store in cool, dry place.

KEEP OUT OF REACH OF CHILDREN:

In case of overdose, get medical help or contact a Poison Control Center right away.

DIRECTIONS:

• 10 drops orally, 3 times a day.

• Consult a health care professional for use in children under 12 years of age.

INACTIVE INGREDIENTS:

Demineralized Water, 25% Ethanol

QUESTIONS:

Distributed by:
BioActive Nutritional, Inc.
1803 N. Wickham Rd.
Melbourne, FL 32935
bioactivenutritional.com

1-800-288-9525

PACKAGE LABEL DISPLAY:

BIOActive Nutritional

PROSTATONE

HOMEOPATHIC

1 FL OZ (30 ml)